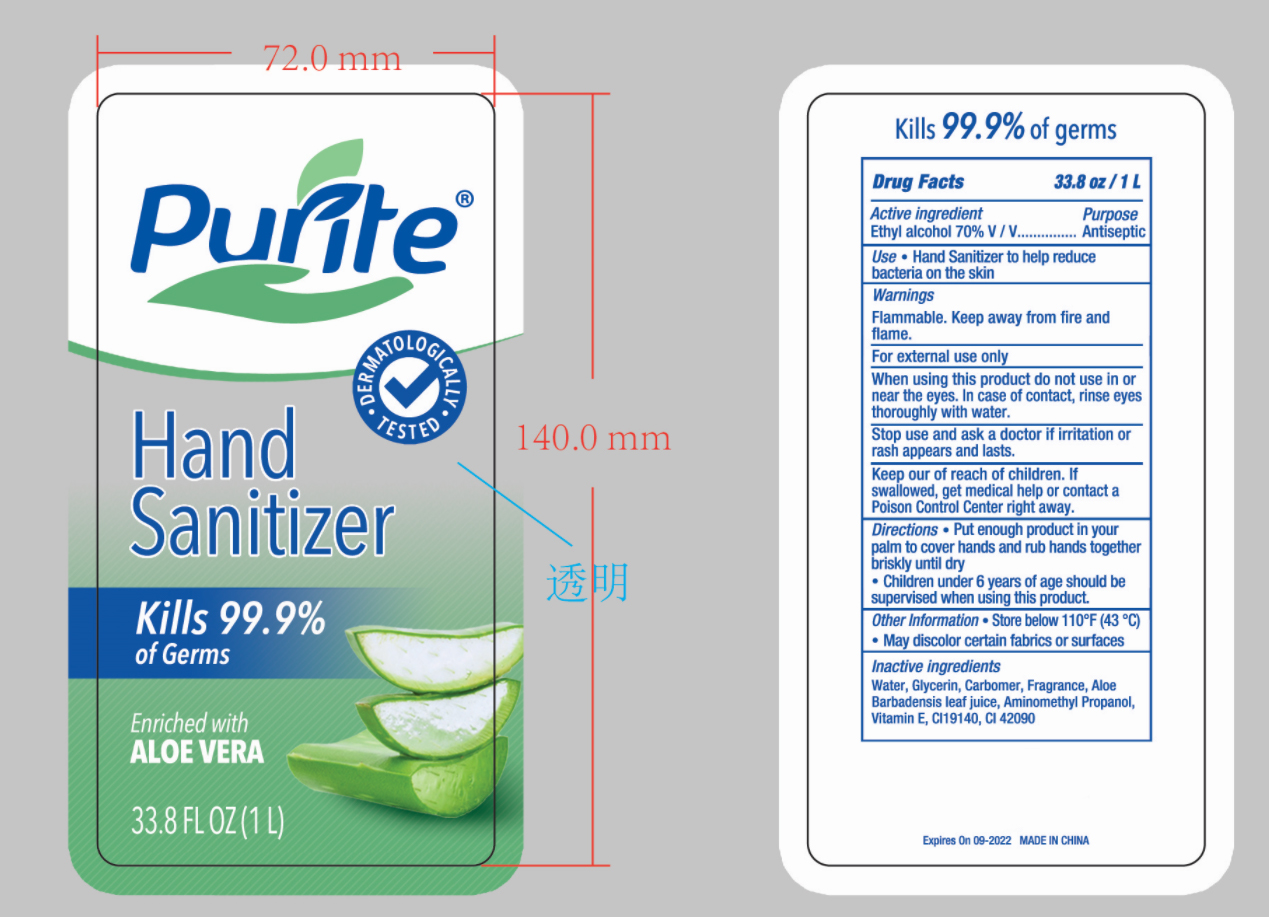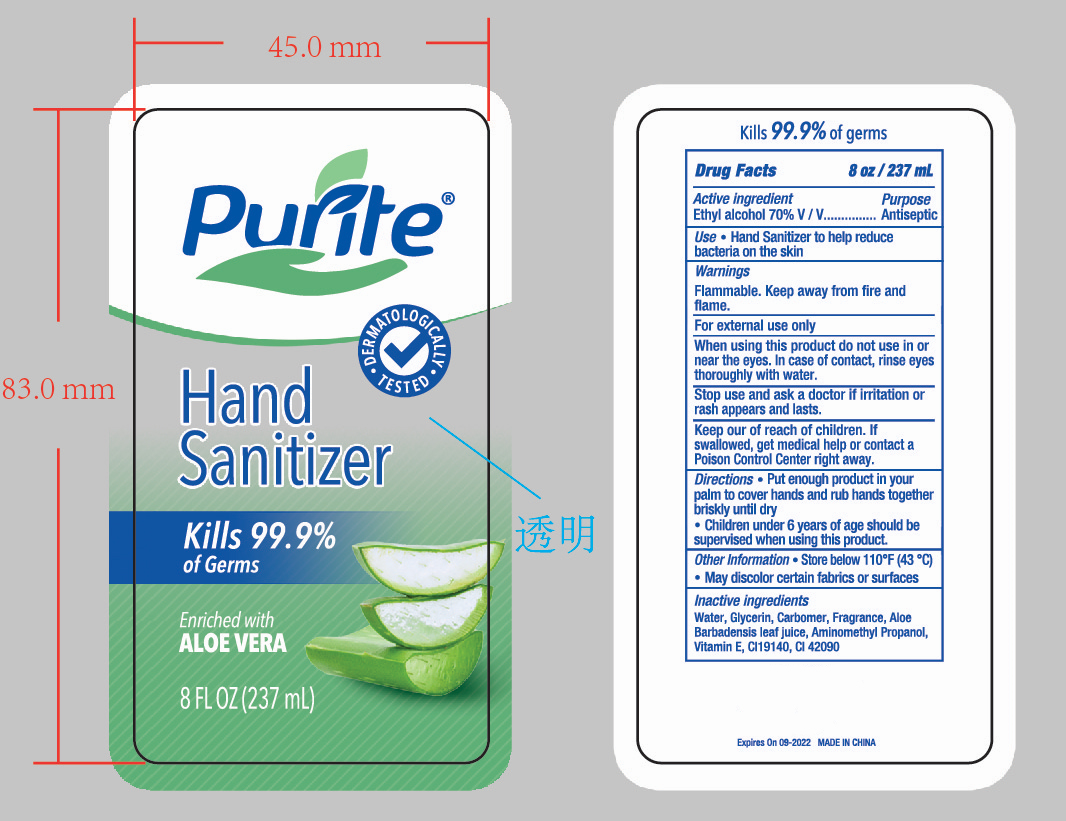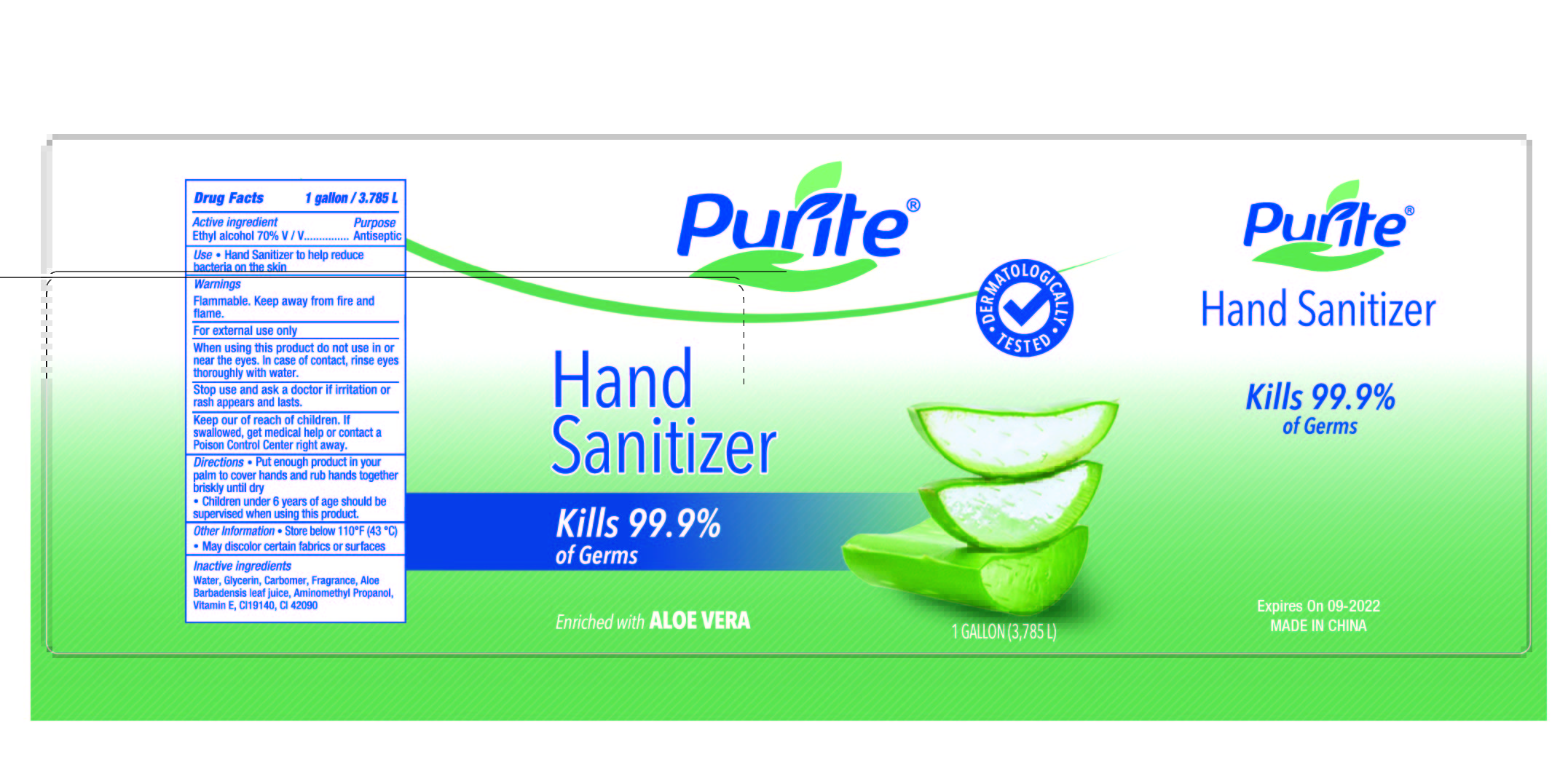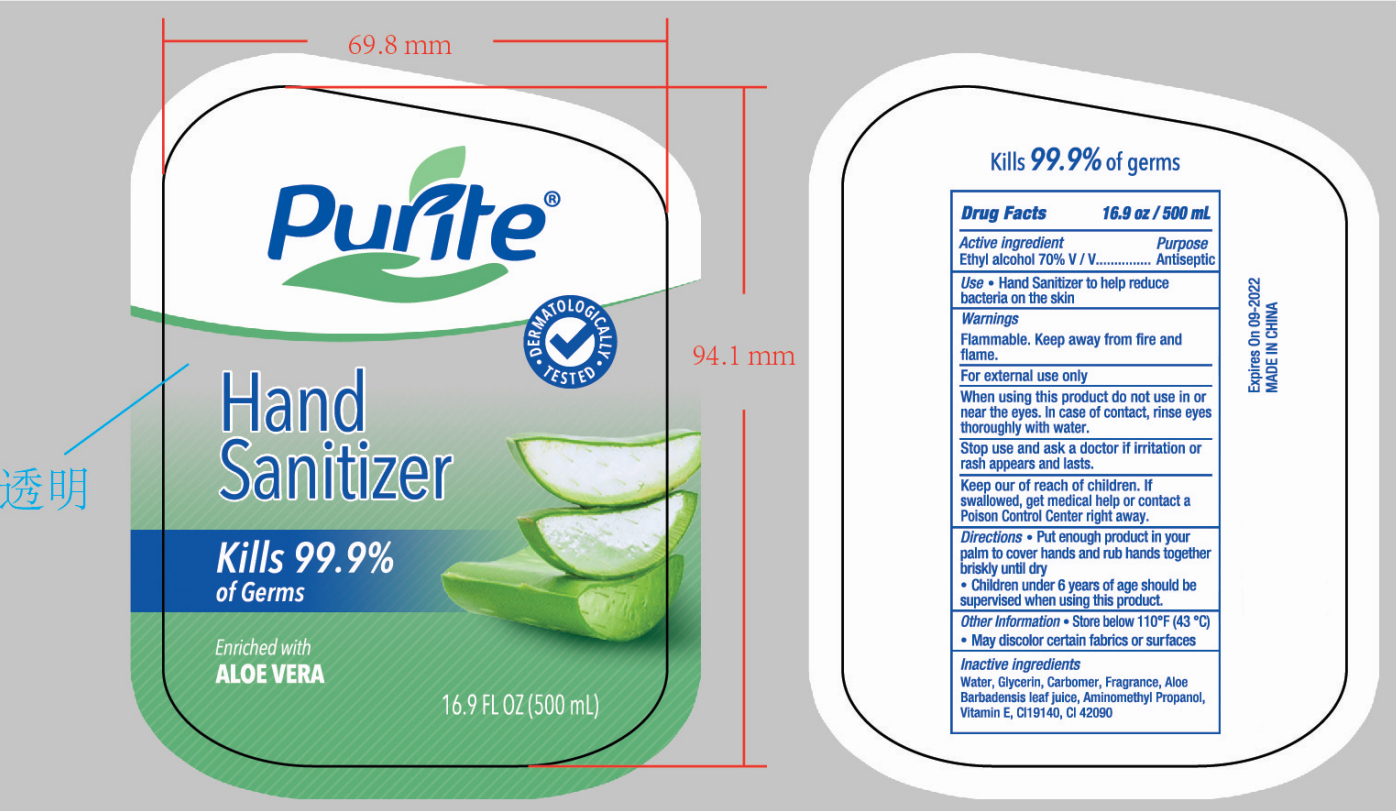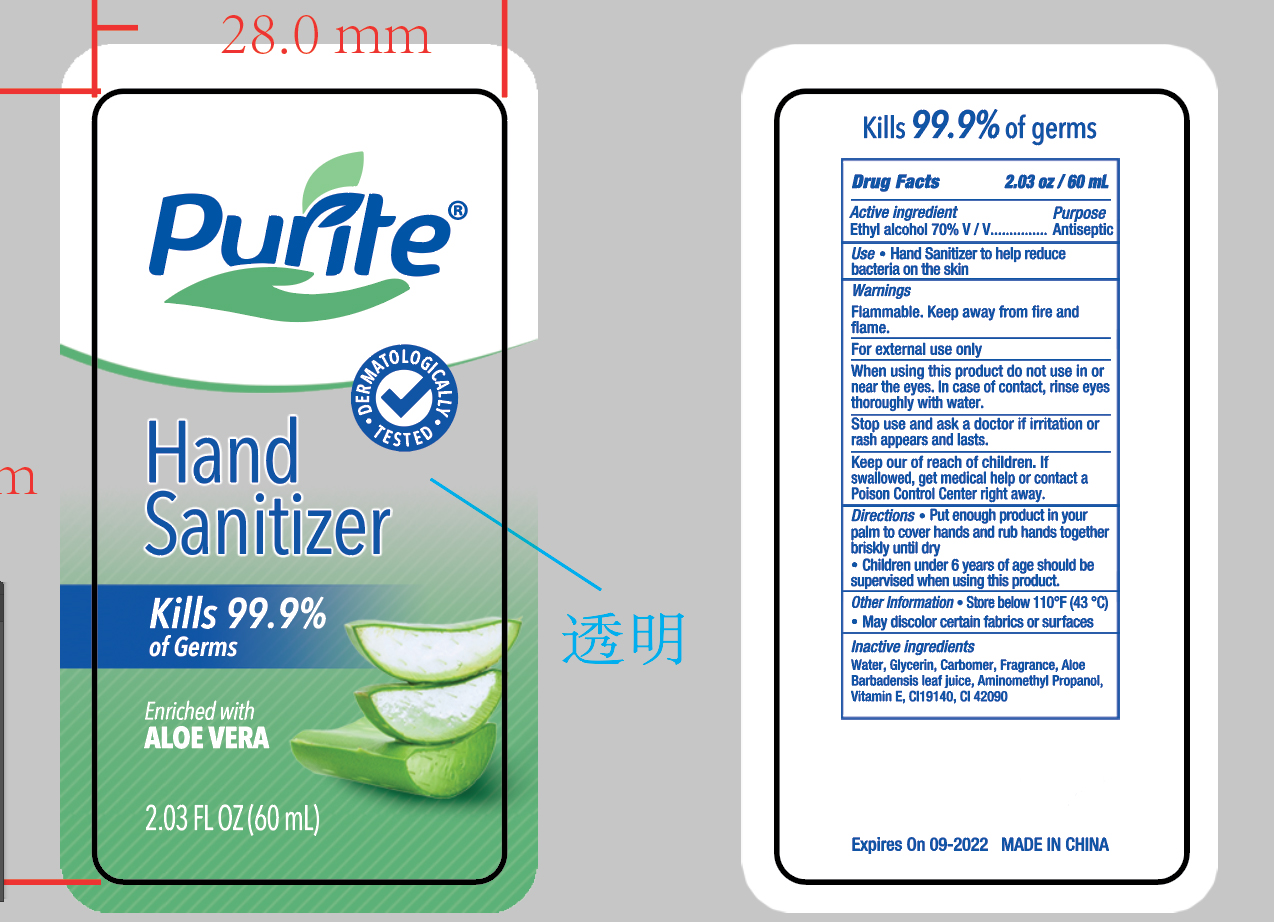 DRUG LABEL: HAND SANITIZER
NDC: 47993-316 | Form: GEL
Manufacturer: NINGBO JIANGBEI OCEAN STAR TRADING CO.,LTD
Category: otc | Type: HUMAN OTC DRUG LABEL
Date: 20201105

ACTIVE INGREDIENTS: ALCOHOL 70 mL/100 mL
INACTIVE INGREDIENTS: WATER; GLYCERIN; CARBOMER 940; ALOE VERA LEAF; AMINOMETHYLPROPANOL; TOCOPHEROL; FD&C YELLOW NO. 5; FD&C BLUE NO. 1

47993-316

Active ingredients

Ethyl alcohol 70% V/V

PURPOSE

Antiseptic

Uses：

- Hand Sanitizer to help reduce bacteria on the skin.

Warnings:

Flammable. Keep away from fire or flame.

For external use only.

When using this product do not use in or near the eyes. In case of contact, rinse eyes thoroughly with water.

Stop use and ask a doctor if irritation or rash appears and lasts.

Keep out of reach of children. If swallowed, get medical help or contact a Poison Control Center right away.

Directions:

- Put enough product in your palm to cover hands and rub hands together briskly until dry.
- Children under 6 years of age should be supervised when using this product.

Other information：

- Store below 110℉(43℃)
- May discolor certain fabrics or surfaces.

Inactive ingredients：

Water,Glycerin,Carbomer,Fragrance,Aloe Barbadensis leaf juice,Aminomethyl Propanol,Vitamin E,CI 19140,CI 42090